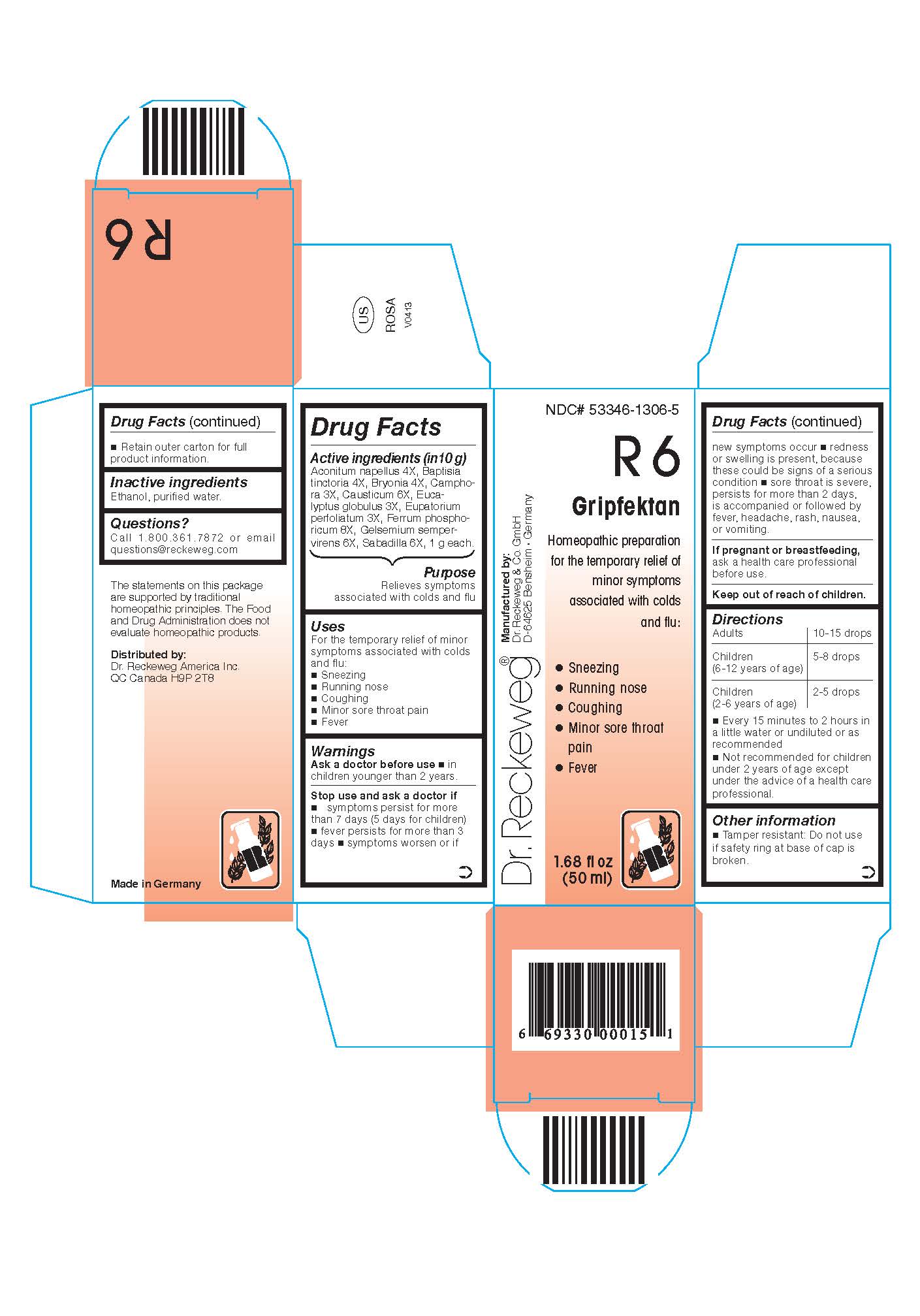 DRUG LABEL: 
                           
NDC: 53346-1306 | Form: LIQUID
Manufacturer: PHARMAZEUTISCHE FABRIK DR. RECKEWEG & CO
Category: homeopathic | Type: HUMAN OTC DRUG LABEL
Date: 20130506

ACTIVE INGREDIENTS: ACONITUM NAPELLUS 4 [hp_X]/50 mL; BAPTISIA TINCTORIA ROOT 4 [hp_X]/50 mL; BRYONIA DIOICA ROOT 4 [hp_X]/50 mL; CAMPHOR (NATURAL) 3 [hp_X]/50 mL; CAUSTICUM 6 [hp_X]/50 mL; EUCALYPTUS GLOBULUS LEAF 3 [hp_X]/50 mL; EUPATORIUM PERFOLIATUM FLOWERING TOP 3 [hp_X]/50 mL; FERRIC PHOSPHATE 8 [hp_X]/50 mL; GELSEMIUM SEMPERVIRENS ROOT 6 [hp_X]/50 mL; SCHOENOCAULON OFFICINALE SEED 6 [hp_X]/50 mL
INACTIVE INGREDIENTS: ALCOHOL; WATER

DR. RECKEWEG R6 Gripfektan

ACTIVE INGREDIENT

Enter section text here

Active ingredients
Aconitum napellus 4X, Baptisia tinctoria 4X, Bryonia 4X, Camphora 3X, Causticum 6X, Eucalyptus globulus 3X, Eupatorium perfoliatum 3X, Ferrum phosphoricum 8X, Gelsemium sempervirens 6X, Sabadilla 6X, 1 g each in 10 g.

PURPOSE

Enter section text here

Purpose
Relieves symptoms associated with colds and flu

Uses
For the temporary relief of minor symptoms associated with colds and flu:
* Sneezing
* Running nose
* Coughing
* Minor sore throat pain
* Fever

Warnings

Ask a doctor before use
* in children younger than 2 years

Stop use and ask a doctor if
* symptoms persist for more than 7 days (5 days for children)
* fever persists for more than 3 days
* symptoms worsen or if new symptoms occur
* redness or swelling is present, because these could be signs of a serious condition
* sore throat is severe, persists for more than 2 days, is accompanied or followed by fever, headache, rash, nausea, or vomiting.

PREGNANCY OR BREAST FEEDING

If pregnant or breastfeeding, ask a health care professional before use.

Keep out of reach of children.

Directions
Adults: 10-15 drops; children (6-12 years of age): 5-8 drops;
children (2-6 years of age): 2-5 drops, every 15 minutes to 2 hours in a little water or undiluted or as recommended.
Not recommended for children under 2 years of age except under the advice of a health care professional.

Other information
* Tamper resistant: Do not use if safety ring at base of cap is broken.
* Retain outer carton for full product instructions.

Inactive ingredients
Ethanol, purified water.

Questions?
Call 1-800-361-7872 or email questions@reckeweg.com

PACKAGE LABEL

NDC# 53346-1306-5
Dr. Reckeweg R6 Gripfektan
Homeopathic preparation for the temporary relief of minor symptoms associated with colds and flu:
* Sneezing
* Running nose
* Coughing
* Minor sore throat pain
* Fever
Manufactured by:
Dr. Reckeweg Co. GmbH
D-64625 Bensheim
Germany
1.68 fl oz
(50 ml)